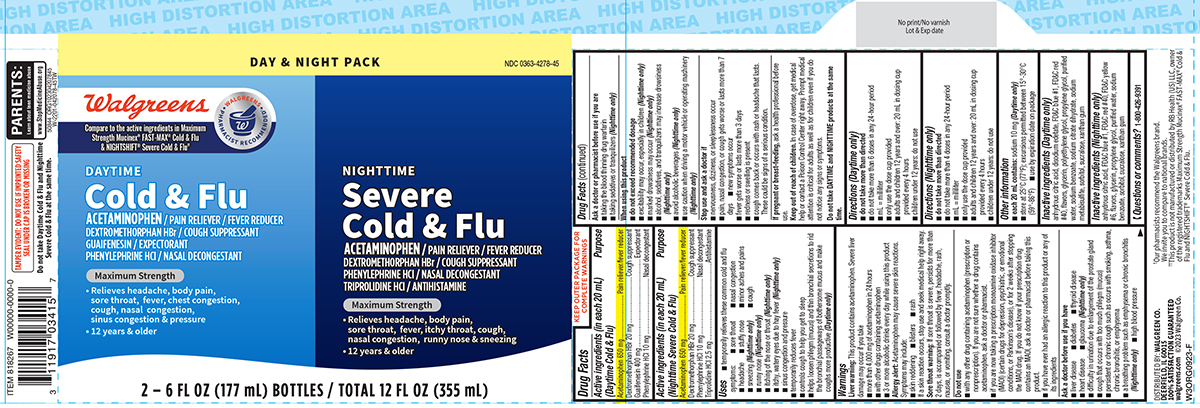 DRUG LABEL: Cold and Flu
NDC: 0363-4278 | Form: KIT | Route: ORAL
Manufacturer: Walgreen Company
Category: otc | Type: HUMAN OTC DRUG LABEL
Date: 20251028

ACTIVE INGREDIENTS: ACETAMINOPHEN 650 mg/20 mL; DEXTROMETHORPHAN HYDROBROMIDE 20 mg/20 mL; GUAIFENESIN 400 mg/20 mL; PHENYLEPHRINE HYDROCHLORIDE 10 mg/20 mL; ACETAMINOPHEN 650 mg/20 mL; DEXTROMETHORPHAN HYDROBROMIDE 20 mg/20 mL; PHENYLEPHRINE HYDROCHLORIDE 10 mg/20 mL; TRIPROLIDINE HYDROCHLORIDE 2.5 mg/20 mL
INACTIVE INGREDIENTS: ANHYDROUS CITRIC ACID; EDETATE DISODIUM; FD&C BLUE NO. 1; FD&C RED NO. 40; GLYCERIN; POLYETHYLENE GLYCOL, UNSPECIFIED; PROPYLENE GLYCOL; WATER; SODIUM BENZOATE; TRISODIUM CITRATE DIHYDRATE; SODIUM METABISULFITE; SORBITOL; SUCRALOSE; XANTHAN GUM; ANHYDROUS CITRIC ACID; FD&C BLUE NO. 1; FD&C RED NO. 40; FD&C YELLOW NO. 6; GLYCERIN; PROPYLENE GLYCOL; WATER; SODIUM BENZOATE; SORBITOL; SUCRALOSE; XANTHAN GUM

Walgreens 44-042078

Active ingredients (in each 20 mL) (Daytime Cold & Flu)

Acetaminophen 650 mg
Dextromethorphan HBr 20 mg
Guaifenesin 400 mg
Phenylephrine HCl 10 mg

Purpose

Pain reliever/fever reducer
Cough suppressant
Expectorant
Nasal decongestant

Active ingredients (in each 20 mL) (Nighttime Severe Cold & Flu)

Acetaminophen 650 mg
Dextromethorphan HBr 20 mg
Phenylephrine HCl 10 mg
Triprolidine HCl 2.5 mg

Purpose

Pain reliever/fever reducer
Cough suppressant
Nasal decongestant
Antihistamine

Uses

- temporarily relieves these common cold and flu symptoms:
  - sore throat
  - nasal congestion
  - stuffy nose
  - minor aches and pains
  - sneezing (Nighttime only)
  - headache
  - cough
  - runny nose (Nighttime only)
  - itching of the nose or throat (Nighttime only)
  - itchy, watery eyes due to hay fever (Nighttime only)
  - sinus congestion and pressure
- temporarily reduces fever
- controls cough to help you get to sleep
- helps loosen phlegm (mucus) and thin bronchial secretions to rid the bronchial passageways of bothersome mucus and make coughs more productive (Daytime only)

Warnings

Liver warning: This product contains acetaminophen. Severe liver damage may occur if you take

- more than 4,000 mg of acetaminophen in 24 hours
- with other drugs containing acetaminophen
- 3 or more alcoholic drinks every day while using this product

Allergy alert: Acetaminophen may cause severe skin reactions. Symptoms may include:

- skin reddening
- blisters
- rash

If a skin reaction occurs, stop use and seek medical help right away.

Sore throat warning: If sore throat is severe, persists for more than 2 days, is accompanied or followed by fever, headache, rash, nausea, or vomiting, consult a doctor promptly.

Do not use

- with any other drug containing acetaminophen (prescription or nonprescription). If you are not sure whether a drug contains acetaminophen, ask a doctor or pharmacist.
- if you are now taking a prescription monoamine oxidase inhibitor (MAOI) (certain drugs for depression, psychiatric, or emotional conditions, or Parkinson’s disease), or for 2 weeks after stopping the MAOI drug. If you do not know if your prescription drug contains an MAOI, ask a doctor or pharmacist before taking this product.
- if you have ever had an allergic reaction to this product or any of its ingredients

Ask a doctor before use if you have

- liver disease
- diabetes
- thyroid disease
- heart disease
- glaucoma (Nighttime only)
- difficulty in urination due to enlargement of the prostate gland
- cough that occurs with too much phlegm (mucus)
- persistent or chronic cough such as occurs with smoking, asthma, chronic bronchitis, or emphysema
- a breathing problem such as emphysema or chronic bronchitis (Nighttime only)
- high blood pressure

Ask a doctor or pharmacist before use if you are

- taking the blood thinning drug warfarin
- taking sedatives or tranquilizers (Nighttime only)

When using this product

- do not exceed recommended dosage
- excitability may occur, especially in children (Nighttime only)
- marked drowsiness may occur (Nighttime only)
- alcohol, sedatives, and tranquilizers may increase drowsiness (Nighttime only)
- avoid alcoholic beverages (Nighttime only)
- use caution when driving a motor vehicle or operating machinery (Nighttime only)

Stop use and ask a doctor if

- nervousness, dizziness, or sleeplessness occur
- pain, nasal congestion, or cough gets worse or lasts more than 7 days
- new symptoms occur
- fever gets worse or lasts more than 3 days
- redness or swelling is present
- cough comes back or occurs with rash or headache that lasts. These could be signs of a serious condition.

If pregnant or breast-feeding,

ask a health professional before use.

Keep out of reach of children.

In case of overdose, get medical help or contact a Poison Control Center right away. Prompt medical attention is critical for adults as well as for children even if you do not notice any signs or symptoms.

Do not take DAYTIME and NIGHTTIME products at the same time.

Directions (Daytime only)

- do not take more than directed
- do not take more than 6 doses in any 24-hour period
- mL = milliliter
- only use the dose cup provided
- adults and children 12 years and over: 20 mL in dosing cup provided every 4 hours
- children under 12 years: do not use

Directions (Nighttime only)

- do not take more than directed
- do not take more than 4 doses in any 24-hour period
- mL = milliliter
- only use the dose cup provided
- adults and children 12 years and over: 20 mL in dosing cup provided every 4 hours
- children under 12 years: do not use

Other information

- each 20 mL contains: sodium 10 mg (Daytime only)
- store at 25°C (77°F); excursions permitted between 15°-30°C (59°-86°F)
- use by expiration date on package

Inactive ingredients (Daytime only)

anhydrous citric acid, disodium edetate, FD&C blue #1, FD&C red #40, flavors, glycerin, polyethylene glycol, propylene glycol, purified water, sodium benzoate, sodium citrate dihydrate, sodium metabisulfite, sorbitol, sucralose, xanthan gum

Inactive ingredients (Nighttime only)

anhydrous citric acid, FD&C blue #1, FD&C red #40, FD&C yellow #6, flavors, glycerin, propylene glycol, purified water, sodium benzoate, sorbitol, sucralose, xanthan gum

Questions or comments?

1-800-426-9391

Principal display panel

DAY & NIGHT PACK
NDC 0363-4278-45

Walgreens
• WALGREENS •
PHARMACIST RECOMMENDED†
Compare to the active ingredients in Maximum
Strength Mucinex® FAST-MAX® Cold & Flu
& NIGHTSHIFT® Severe Cold & Flu††

DAYTIME
Cold & Flu
ACETAMINOPHEN / PAIN RELIEVER / FEVER REDUCER
DEXTROMETHORPHAN HBr / COUGH SUPPRESSANT
GUAIFENESIN / EXPECTORANT
PHENYLEPHRINE HCl / NASAL DECONGESTANT

Maximum Strength

• Relieves headache, body pain,
sore throat, fever, chest congestion,
cough, nasal congestion,
sinus congestion & pressure
• 12 years & older

NIGHTTIME
Severe
Cold & Flu

ACETAMINOPHEN / PAIN RELIEVER / FEVER REDUCER
DEXTROMETHORPHAN HBr / COUGH SUPPRESSANT
PHENYLEPHRINE HCl / NASAL DECONGESTANT
TRIPROLIDINE HCl / ANTIHISTAMINE

Maximum Strength

• Relieves headache, body pain,
sore throat, fever, itchy throat, cough,
nasal congestion, runny nose & sneezing
• 12 years & older

2 – 6 FL OZ (177 mL) BOTTLES / TOTAL 12 FL OZ (355 mL)
TAMPER EVIDENT: DO NOT USE IF IMPRINTED SAFETY
SEAL UNDER CAP IS BROKEN OR MISSING
Do not take Daytime Cold & Flu and Nighttime
Severe Cold & Flu at the same time.

PARENTS:
Learn about teen medicine abuse
www.StopMedicineAbuse.org

DISTRIBUTED BY: WALGREEN CO.
DEERFIELD, IL 60015
100% SATISFACTION GUARANTEED
walgreens.com ©2023 Walgreen Co.

†Our pharmacists recommend the Walgreens brand.
We invite you to compare to national brands.
††This product is not manufactured or distributed by RB Health (US) LLC, owner
of the registered trademarks Maximum Strength Mucinex® FAST-MAX® Cold &
Flu and NIGHTSHIFT® Severe Cold & Flu.

50844 ORG102304207845

Walgreens 44-042078